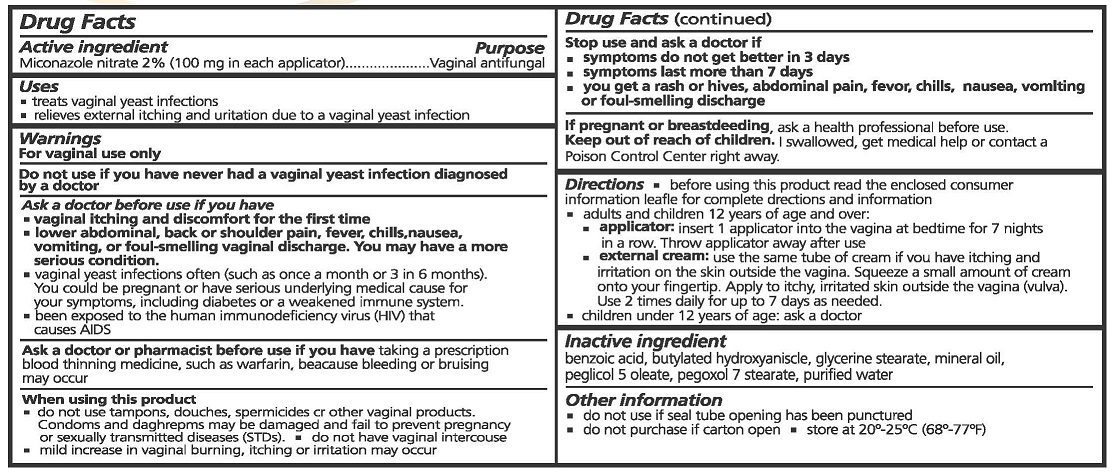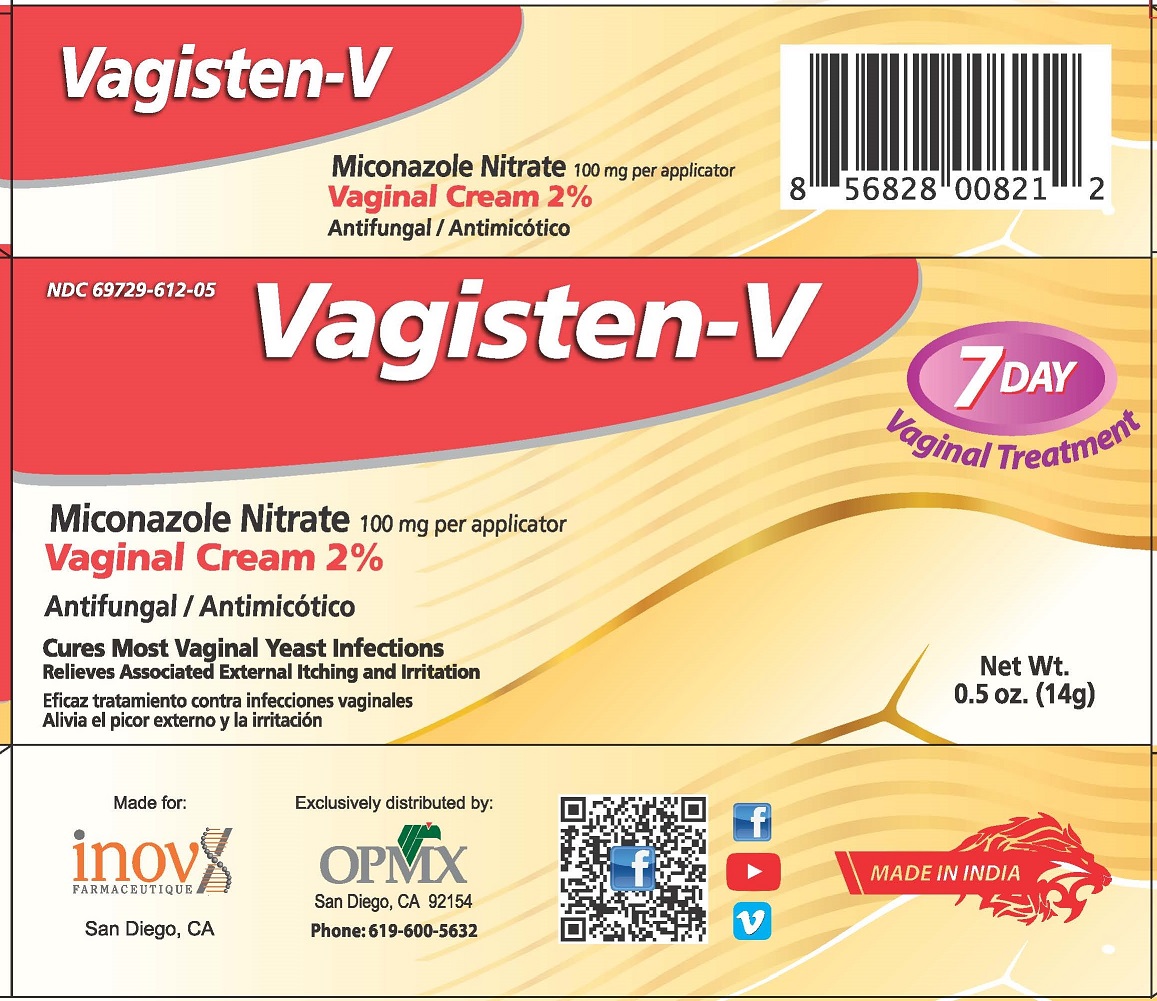 DRUG LABEL: VAGISTEN-V
NDC: 69729-612 | Form: CREAM
Manufacturer: OPMX LLC
Category: otc | Type: HUMAN OTC DRUG LABEL
Date: 20240904

ACTIVE INGREDIENTS: MICONAZOLE NITRATE 2 g/100 g
INACTIVE INGREDIENTS: BENZOIC ACID; BUTYLATED HYDROXYANISOLE; GLYCERYL MONOSTEARATE; MINERAL OIL; PEG-5 OLEATE; PEGOXOL 7 STEARATE; WATER

OPMX (as PLD) - Vagisten-V (69729-612)

ACTIVE INGREDIENTS

MICONOZOLE NITRATE 2% (100 MG IN EACH APPLICATOR)

PURPOSE

VAGINAL ANTIFUNGAL

USES

- TREATS VAGINAL YEAST INFECTIONS
- RELIEVES EXTERNAL ITCHING AND URINATION DUE TO VAGINAL YEAST INFECTION

WARNINGS

FOR VAGINAL USE ONLY.

DO NOT USE IF YOU HAVE NEVER HAD A VAGINAL YEAST INFECTION DIAGNOSED BY A DOCTOR.

ASK A DOCTOR BEFORE USE IF YOU HAVE

- VAGINAL ITCHING AND DISCOMFORT FOR FIRST TIME
- LOWER ABDOMINAL, BACK OR SHOULDER PAIN, FEVER, CHILLS, NASEA, VOMITING, OR FOUL-SMELLING VAGINAL DISCHARGE. YOU MAY HAVE A MORE SERIOUS CONDITION.
- VAGINAL YEAST INFECTIONS OFTEN (SUCH AS ONCE A MONTH OR 3 IN 6 MONTHS). YOU COULD BE PREGNANT OR HAVE SERIOUS UNDERLYING MEDICAL CAUSE FOR YOUR SYMPTOMS, INCLUDING DIABETES OR A WEAKENED IMMUNE SYSTEM.
- BEEN EXPOSED TO THE HUMAN IMMUNODEFICIENCY VIRUS (HIV) THAT CAUSES AIDS.

ASK A DOCTOR OR PHARMACIST BEFORE USE IF YOU HAVE TAKEN A PRESCRIPTION BLOOD THINNING MEDICINE, SUCH AS WARFARIN, BECAUSE BLEEDING OR BRUISING MAY OCCUR.

WHEN USING THIS PRODUCT

- DO NOT USE TAMPONS, DOUCHES, SPERMACIDES OR OTHER VAGINAL PRODUCTS. CONDOMS AND DIAPHRAGMS MAY BE DAMAGED OR FAIL TO PREVENT PREGNANCY OR SEXUALLY TRANSMITTED DISEASES (STDS).
- DO NOT HAVE VAGINAL INTERCOURSE
- MILD INCREASE IN VAGINAL BURNING, ITCHING OR IRRITATION MAY OCCUR.

STOP USE AND ASK A DOCTOR IF

- SYMPTOMS DO NOT GET BETTER IN 3 DAYS
- SYMPTOMS LAST MORE THAN 7 DAYS
- YOU GET A RASH OR HIVESS, ABDOMINAL PAIN, FEVER, CHILLS, NAUSEA, VOMITING OR FOUL-SMELLING DISCHARGE

IF PREGNANT OR BREAST FEEDING, ASK A HEALTH PROFESSIONAL BEFORE USE.

Keep out of reach of children

- If swallowed get medical help or contact Poison Control Center right away.

DIRECTIONS

- BEFORE USING THIS PRODUCT READ THE ENCLOSED CONSUMER INFORMATION LEAFLET FOR COMPLETE DIRECTIONS AND INFORMATION
- ADULTS AND CHILDREN 12 YEARS OF AGE OR OVER:
- APPLICATOR: INSERT 1 APPLICATOR INTO THE VAGINA AT BEDTIME FOR 7 NIGHTS IN A ROW. THROW APPLICATOR AWAY AFTER USE.
- EXTERNAL CREAM: USE THE SAME TUBE OF CREAM IF YOU HAVE ITCHING AND IRRITATION ON THE SKIN OUTSIDE THE VAGINA. SQUEEZE A SMALL AMOUNT OF CREAM ONTO YOUR FINGERTIP. APPLY TO ITCHY, IRRITATED SKIN OUTSIDE THE VAGINA (VULVA). USE 2 TIMES DAILY FOR UP TO 7 DAYS AS NEEDED.
- CHILDREN UNDER 12 YEARS OF AGE: ASK A DOCTOR.

INACTIVE INGREDIENTS

BENZOIC ACID, BUTYLATED HYDROXYANISOLE, GLYCERINE STEARATE, MINERAL OIL, PEGLICOL 5 OLEATE, PEGOXOL 7 STEARATE, PURIFIED WATER

OTHER INFORMATION

- DO NOT USE IF SEAL TUBE OPENING HAS BEEN PUNCTURED
- DO NOT PURCHASE IF CARTON OPEN
- STORE AT 20° - 25°C (68°F - 77°F)